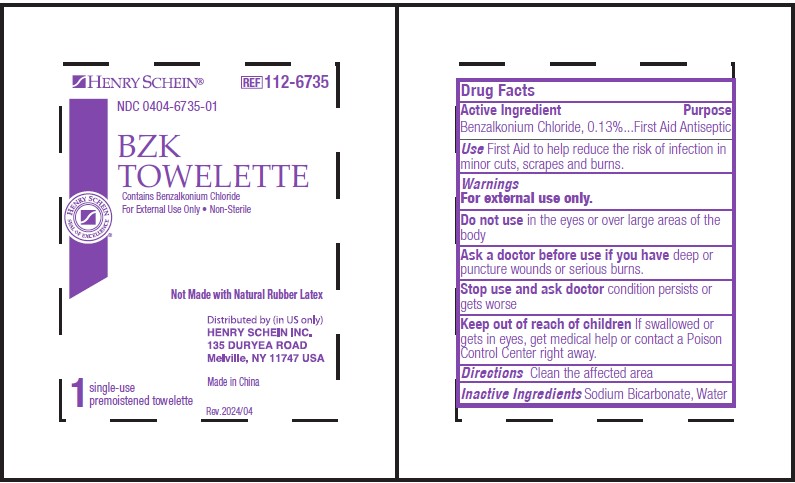 DRUG LABEL: BZK
NDC: 0404-6735 | Form: LIQUID
Manufacturer: Henry Schein Inc.
Category: otc | Type: HUMAN OTC DRUG LABEL
Date: 20240402

ACTIVE INGREDIENTS: BENZALKONIUM CHLORIDE 0.0013 g/1 g
INACTIVE INGREDIENTS: WATER; SODIUM BICARBONATE

ANTISEPTIC – Benzalkonium chloride liquid
Henry Schein

Drug Facts

Active ingredients

Benzalkonium Chloride 0.13%

Purpose

First Aid Antiseptic

Uses

- First Aid to help reduce the risk of infection in minor cuts, scrapes and burns

RECENT MAJOR CHANGES

Updaed Indications & USage section to be in line with the OTC Monograph

Warnings

For external use only.

Do not use in the eyes. If this happens, rinse thoroughly with water.

Stop use and ask a doctor if irritation or redness develop and persists for more than 72 hours

Keep out of reach of children If swallowed get medical help or contact a Poison Control Center right away

Directions

- Tear open packet, unfold and use as a washcloth. Allow hands to dry without wiping.

Inactive ingredients purified water, alcohol

Made in USA

PRINCIPAL DISPLAY PANEL – packet label

Henry Schein REF112-6735

NDC 0404-6735-01

BZK TOWELETTE

Contains Benzalkonium Chloride

For External Use Only • Non-Sterile

Not Made with Natural Rubber Latex

1 single-use, premoistened towelette

Distributed by (in US only)
HENRY SCHEIN, Inc. 135 Duryea Road

Melville, NY 11747 USA

Made in China

Rev.2024/04